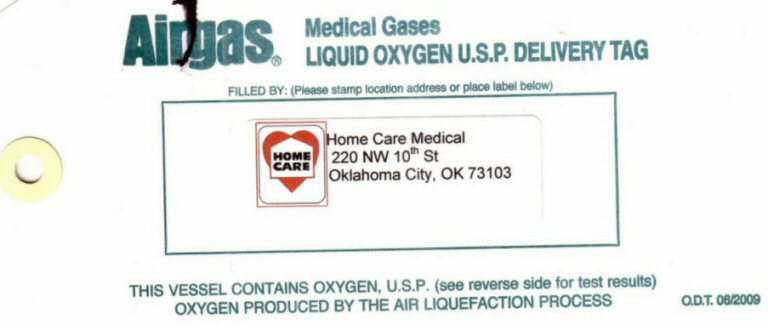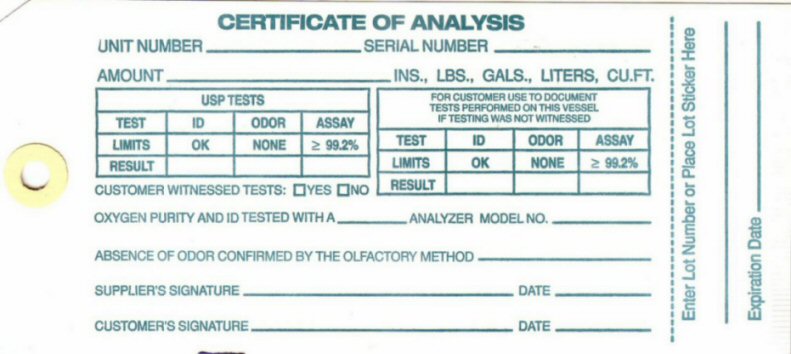 DRUG LABEL: OXYGEN
NDC: 52200-001 | Form: GAS
Manufacturer: Home Care Medical LLC
Category: prescription | Type: HUMAN PRESCRIPTION DRUG LABEL
Date: 20100101

ACTIVE INGREDIENTS: OXYGEN 99 L/100 L

CERTIFICATE OF ANALYSIS UNIT NUMBER___________ SERIAL NUMBER___________ AMOUNT_________________INS, LBS, LITERS, CU FT.

USP TESTS

TEST ID ODOR ASSAY

LIMITS OK NONE 99.2%

RESULT __ _____ _____

FOR CUSTOMERS USE TO DOCUMENT TESTS PERFORMED ON THIS VESSEL IF TESTING WAS NOT WITNESSED

TEST ID ODOR ASSAY

LIMITS OK NONE 99.2%

RESULT __ _____ _____

CUSTOMER WITNESSED TESTS? _YES ___NO

OXYGEN PURITY AND ID TESTED WITH A __________ ANALYZER MODEL NO_________ ABSENCE OF ODOR CONFIRMED BY THE OLIFACTORY METHOD _________ SUPPLIERS SIGNATURE_____________________ DATE____________ CUSTOMERS SIGNATURE_____________DATE____________ ENTER LOT NUMBER AND PLACE STICKER HERE________________ EXPIRATION DATE__________

MEDICAL GASES LIQUID OXYGEN U.S.P. DELIVERY TAG FILLED BY: (PLEASE STAMP LOCATION ADDRESS OR PLACE LABEL BELOW) THIS VESSEL CONTAINS OXYGEN U.S.P. (SEE REVERSE SIDE FOR TEST RESULTS) OXYGEN PRODUCED BY THE AIR LIQUEFACTION METHOD